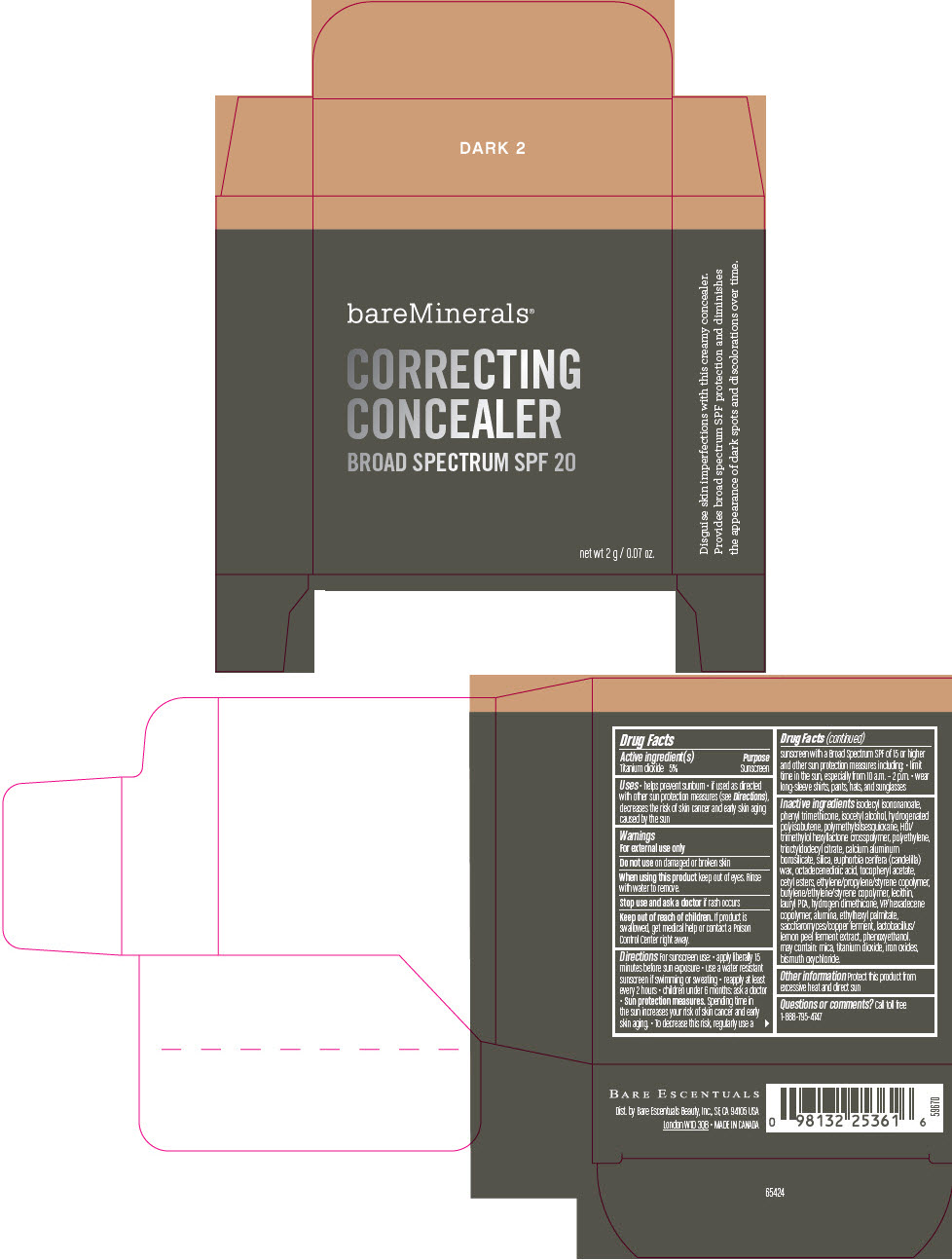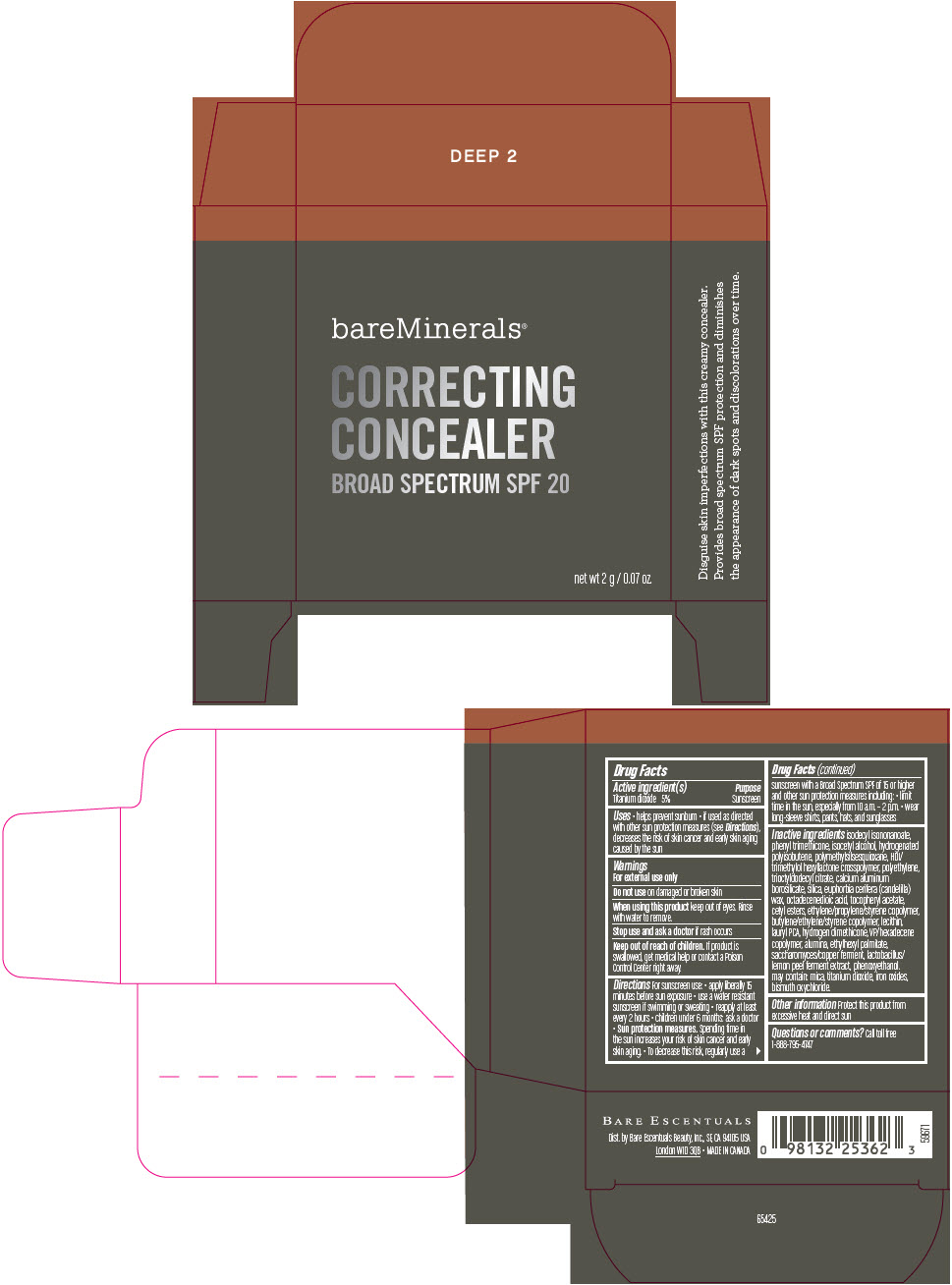 DRUG LABEL: BAREMINERALS SPF 20 CORRECTING CONCEALER
NDC: 98132-001 | Form: CREAM
Manufacturer: Orveon Global US LLC
Category: otc | Type: HUMAN OTC DRUG LABEL
Date: 20231004

ACTIVE INGREDIENTS: TITANIUM DIOXIDE 0.1 g/2 g
INACTIVE INGREDIENTS: PHENYL TRIMETHICONE; ISODECYL ISONONANOATE; TRIOCTYLDODECYL CITRATE; .ALPHA.-TOCOPHEROL ACETATE, DL-; PHENOXYETHANOL; HYDROGEN DIMETHICONE (13 CST); SILICON DIOXIDE; ALUMINUM OXIDE; ISOCETYL ALCOHOL; HYDROGENATED POLYBUTENE (1300 MW); HIGH DENSITY POLYETHYLENE; OCTADECENEDIOIC ACID; CETYL ESTERS WAX; CANDELILLA WAX; VINYLPYRROLIDONE/HEXADECENE COPOLYMER; LAURYL PIDOLATE; ETHYLHEXYL PALMITATE; HEXAMETHYLENE DIISOCYANATE/TRIMETHYLOL HEXYLLACTONE CROSSPOLYMER; MICA; FERRIC OXIDE RED; POLYMETHYLSILSESQUIOXANE (4.5 MICRONS); CALCIUM ALUMINUM BOROSILICATE; BISMUTH OXYCHLORIDE

BAREMINERALS® SPF 20 CORRECTING CONCEALER

Drug Facts

Active ingredient(s)

Titanium dioxide 5%

Purpose

Sunscreen

Uses

- helps prevent sunburn
- if used as directed with other sun protection measures (see Directions), decreases the risk of skin cancer and early skin aging caused by the sun

Warnings

For external use only

Do not use on damaged or broken skin

When using this product keep out of eyes. Rinse with water to remove.

Stop use and ask a doctor if rash occurs

Keep out of reach of children. If product is swallowed, get medical help or contact a Poison Control Center right away.

Directions

For sunscreen use:

- apply liberally 15 minutes before sun exposure
- use a water resistant sunscreen if swimming or sweating
- reapply at least every 2 hours
- children under 6 months: ask a doctor
- Sun protection measures. Spending time in the sun increases your risk of skin cancer and early skin aging.
- To decrease this risk, regularly use a sunscreen with a Broad Spectrum SPF of 15 or higher and other sun protection measures including:
  - limit time in the sun, especially from 10 a.m. – 2 p.m.
  - wear long-sleeve shirts, pants, hats, and sunglasses

Inactive ingredients

isodecyl isononanoate, phenyl trimethicone, isocetyl alcohol, hydrogenated polyisobutene, polymethylsilsesquioxane, HDI/trimethylol hexyllactone crosspolymer, polyethylene, trioctyldodecyl citrate, calcium aluminum borosilicate, silica, euphorbia cerifera (candelilla) wax, octadecenedioic acid, tocopheryl acetate, cetyl esters, ethylene/propylene/styrene copolymer, butylene/ethylene/styrene copolymer, lecithin, lauryl PCA, hydrogen dimethicone, VP/hexadecene copolymer, alumina, ethylhexyl palmitate, saccharomyces/copper ferment, lactobacillus/lemon peel ferment extract, phenoxyethanol.

may contain: mica, titanium dioxide, iron oxides, bismuth oxychloride.

Other information

Protect this product from excessive heat and direct sun

Questions or comments?

Call toll free 1-888-795-4747

Dist. by Bare Escentuals Beauty, Inc., SF, CA 94105 USA

PRINCIPAL DISPLAY PANEL - 2 g Container Carton - Dark 2

bareMinerals®

CORRECTING
CONCEALER
BROAD SPECTRUM SPF 20

net wt 2 g / 0.07 oz.

PRINCIPAL DISPLAY PANEL - 2 g Container Carton - Deep 2

bareMinerals®

CORRECTING
CONCEALER
BROAD SPECTRUM SPF 20

net wt 2 g / 0.07 oz.